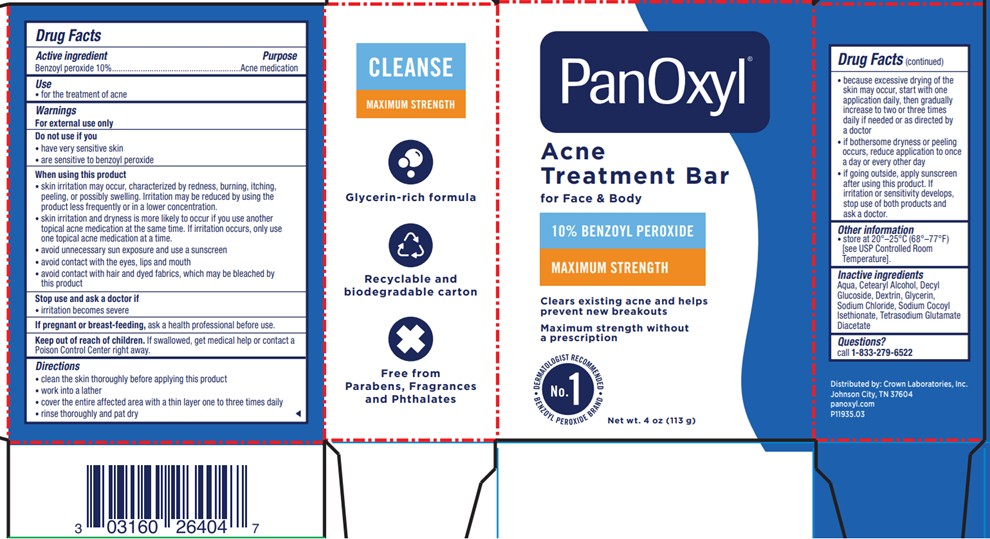 DRUG LABEL: PanOxyl
NDC: 0316-0264 | Form: SOAP
Manufacturer: Crown Laboratories
Category: otc | Type: HUMAN OTC DRUG LABEL
Date: 20260112

ACTIVE INGREDIENTS: BENZOYL PEROXIDE 12.6 g/113 g
INACTIVE INGREDIENTS: ICODEXTRIN; DECYL GLUCOSIDE; GLYCERIN; SODIUM CHLORIDE; WATER; SODIUM COCOYL ISETHIONATE; TETRASODIUM GLUTAMATE DIACETATE; CETOSTEARYL ALCOHOL

Panoxyl Acne Treatment Bar

Active ingredient

Benzoyl peroxide 10%

Purpose

Acne medication

Use

- for the treatment of acne

Warnings

For external use only

Do not use if you

- have very sensitive skin
- are sensitive to benzoyl peroxide

When using this product

- skin irritation may occur, characterized by redness, burning, itching, peeling, or possibly swelling. Irritation may be reduced by using the product less frequently or in a lower concentration.
- skin irritation and dryness is more likely to occur if you use another topical acne medication at the same time. If irritation occurs, only use one topical acne medication at a time
- avoid unnecessary sun exposure and use a sunscreen
- avoid contact with the eyes, lips and mouth
- avoid contact with hair and dyed fabrics, which may be bleached by this product

Stop use and ask a doctor if

- irritation becomes severe

If pregnant or breast-feeding,

ask a health professional before use.

Keep out of reach of children.

If swallowed, get medical help or contact a Poison Control Center right away.

Directions

- clean the skin thoroughly before applying this product
- work into a lather
- cover the entire affected area with a thin layer and rinse thoroughly one to three times daily
- rinse thoroughly and pat dry
- because excessive drying of the skin may occur, start with one application daily, then gradually increase to two or three times daily if needed or as directed by a doctor
- if bothersome dryness or peeling occurs, reduce application to once a day or every other day
- if going outside, apply sunscreen after using this product. If irritation or sensitivity develops, stop use of both products and ask a doctor.

Other information

- Store at 20o - 25oC (68o - 77oF) [see USP Controlled Room Temperature].

Inactive ingredients

Aqua, Cetearyl Alcohol, Decyl Glucoside, Dextrin, Glycerin, Sodium Chloride, Sodium Cocoyl Isethionate, Tetrasodium Glutamate
Diacetate

Questions?

call 1-833-279-6522

Panoxyl Acne Treatmet Bar Carton

PanOxyl®

Acne Treatment Bar

for Face & Body

10% BENZOYL PEROXIDE

MAXIMUM STRENGTH

Clears existing acne and helps prevent new breakouts

Maximum strength without a prescription

No. 1 DERMATOLOGIST RECOMMENDED BENZOYL PEROXIDE BRAND

Net wt. 4 oz (113 g)